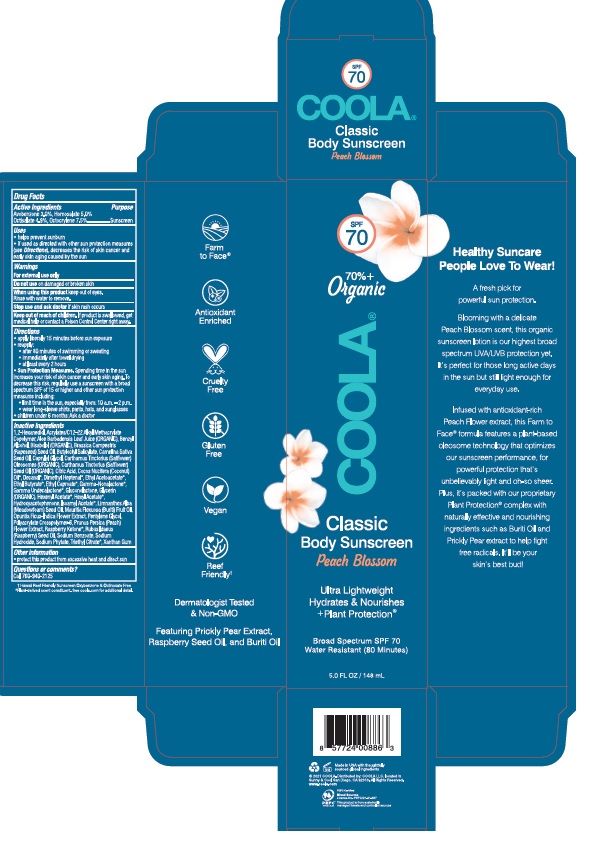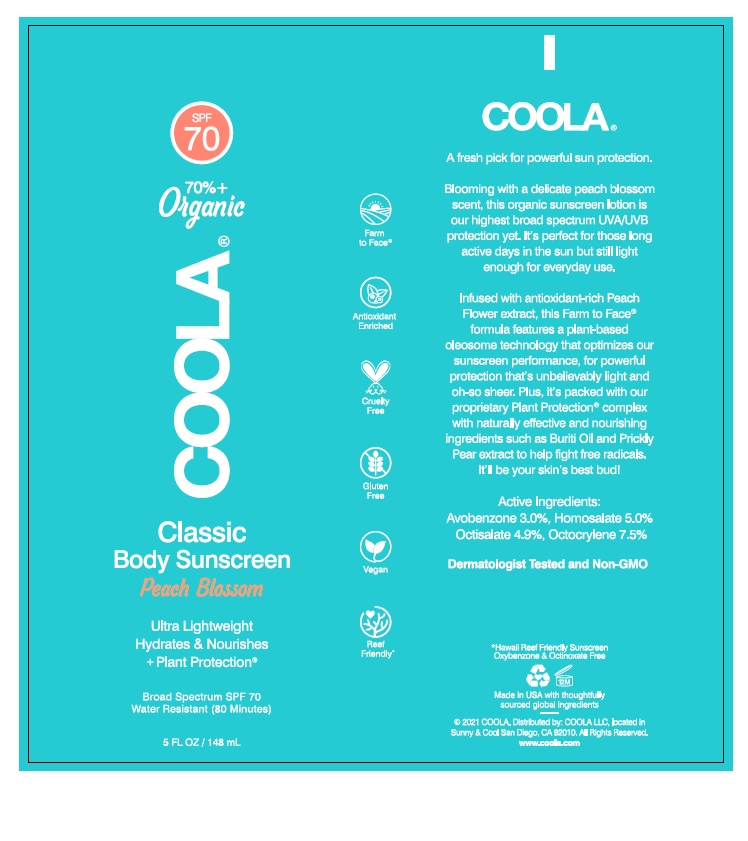 DRUG LABEL: COOLA Classic Body Sunscreen SPF 70 - Peach Blossom
NDC: 79753-015 | Form: CREAM
Manufacturer: COOLA LLC
Category: otc | Type: HUMAN OTC DRUG LABEL
Date: 20231220

ACTIVE INGREDIENTS: AVOBENZONE 3.0 g/100 mL; HOMOSALATE 5.0 g/100 mL; OCTISALATE 4.9 g/100 mL; OCTOCRYLENE 7.5 g/100 mL
INACTIVE INGREDIENTS: 1,2-HEXANEDIOL; BUTYL ACRYLATE/C16-C20 ALKYL METHACRYLATE/METHACRYLIC ACID/METHYL METHACRYLATE COPOLYMER; ALOE VERA LEAF; BENZYL ALCOHOL; LEVOMENOL; BRASSICA RAPA SUBSP. OLEIFERA OIL; BUTYLOCTYL SALICYLATE; CAMELINA SATIVA SEED OIL; CAPRYLYL GLYCOL; CARTHAMUS TINCTORIUS (SAFFLOWER) OLEOSOMES; SAFFLOWER OIL; CITRIC ACID MONOHYDRATE; COCONUT OIL; DECANAL; 2,6-DIMETHYL-5-HEPTENAL; ETHYL ACETOACETATE; ETHYL BUTYRATE; ETHYL CAPROATE; .GAMMA.-NONALACTONE; .GAMMA.-UNDECALACTONE; GLUCONOLACTONE; GLYCERIN; HEXENYL ACETATE, (2Z)-; HEXYL ACETATE; HYDROXYACETOPHENONE; ISOAMYL ACETATE; MEADOWFOAM SEED OIL; MAURITIA FLEXUOSA FRUIT OIL; OPUNTIA FICUS-INDICA LEAF; PENTYLENE GLYCOL; AMMONIUM ACRYLOYLDIMETHYLTAURATE, DIMETHYLACRYLAMIDE, LAURYL METHACRYLATE AND LAURETH-4 METHACRYLATE COPOLYMER, TRIMETHYLOLPROPANE TRIACRYLATE CROSSLINKED (45000 MPA.S); PRUNUS PERSICA FLOWER; 4-(P-HYDROXYPHENYL)-2-BUTANONE; RASPBERRY SEED OIL; SODIUM BENZOATE; SODIUM HYDROXIDE; PHYTATE SODIUM; TRIETHYL CITRATE; XANTHAN GUM

COOLA Classic Body Sunscreen SPF 70 - Peach Blossom

Drug Facts

Active Ingredients

Avobenzone 3.0%, Homosalate 5.0%, Octisalate 4.9%, Octocrylene 7.5%

Purpose

Suncreen

Uses

- helps prevent sunburn

- if used as directed with other sun protection measures

(see Directions), decreases the risk of skin cancer and

early skin aging caused by the sun

Warnings

For external use only

Do not use on damaged or broken skin

When using this product keep out of eyes.

Rinse with water to remove.

Do not use on damaged or broken skin

Stop use and ask doctor if skin rash occurs

Keep out of reach of children. If product is swallowed, get

medical help or contact a Poison Control Center right away.

Directions
• apply liberally 15 minutes before sun exposure.
• reapply:
● after 80 minutes of swimming or sweating
● immediately after towel drying
● at least every 2 hours
Sun Protection Measures. Spending time in the sun
increases your risk of skin cancer and early skin aging. To
decrease this risk, regularly use a sunscreen with a broad
spection SPF of 15 or higher and other sun protection
measures including:
● limit time in the sun, especially from: 10 a.m. - 2 p.m.
● wear long-sleeve shirts, pants, hats, and sunglasses
●Children under 6 months: Ask a doctor

Inactive Ingredients
1,2-Hexanediol, Acrylates/C12-22 Alkyl Methacrylate Copolymer, Aloe Barbadensis Leaf Juice (ORGANIC), Benzyl Alcohol, Bisabolol (ORGANIC), Brassica Campestris (Rapeseed) Seed Oil, Butyloctyl Salicylate, Camelina Sativa Seed Oil, Caprylyl Glycol, Carthamus Tinctorius (Safflower) Oleosomes (ORGANIC), Carthamus Tinctorius (Safflower) Seed Oil (ORGANIC), Citric Acid, Cocos Nucifera (Coconut) Oil*, Decanal*, Dimethyl Heptenal*, Ethyl Acetoacetate*, Ethyl Butyrate*, Ethyl Caproate*, Gamma-Nonalactone*, Gamma Undecalactone*, Gluconolactone, Glycerin (ORGANIC), Hexenyl Acetate*, Hexyl Acetate*, Hydroxyacetophenone, Isoamyl Acetate*, Limnanthes Alba (Meadowfoam) Seed Oil, Mauritia Flexuosa (Buriti) Fruit Oil, Opuntia Ficus-Indica Flower Extract, Pentylene Glycol, Polyacrylate Crosspolymer-6, Prunus Persica (Peach) Flower Extract, Raspberry Ketone*, Rubus Idaeus (Raspberry) Seed Oil, Sodium Benzoate, Sodium Hydroxide, Sodium Phytate, Triethyl Citrate*, Xanthan Gum

Other information

- protect this product from excessive heat and direct sun

Questions or comments?
Call 760-940-2125

COOLA Label

SPF

70

70%+

Organic

COOLA®

Classic

Body Sunscreen

Peach Blossom

Ultra Lightweight

Hydrates & Nourishes

+Plant Protection®

Broad Spectrum SPF 70

Water Resistant (80 Minutes)

5.0 FL OZ / 148 mL

©2021 COOLA. Distributed by: COOLA LLC, located in

Sunny & Cool San Diego, CA 92010. All Rights Reserved.

Hawaii Reef Friendly Sunscreen Oxybenzone & Octinoxate Free
*Plant-derived scent constituent. See coola.com for additional detail.

Carton

Bottle

res